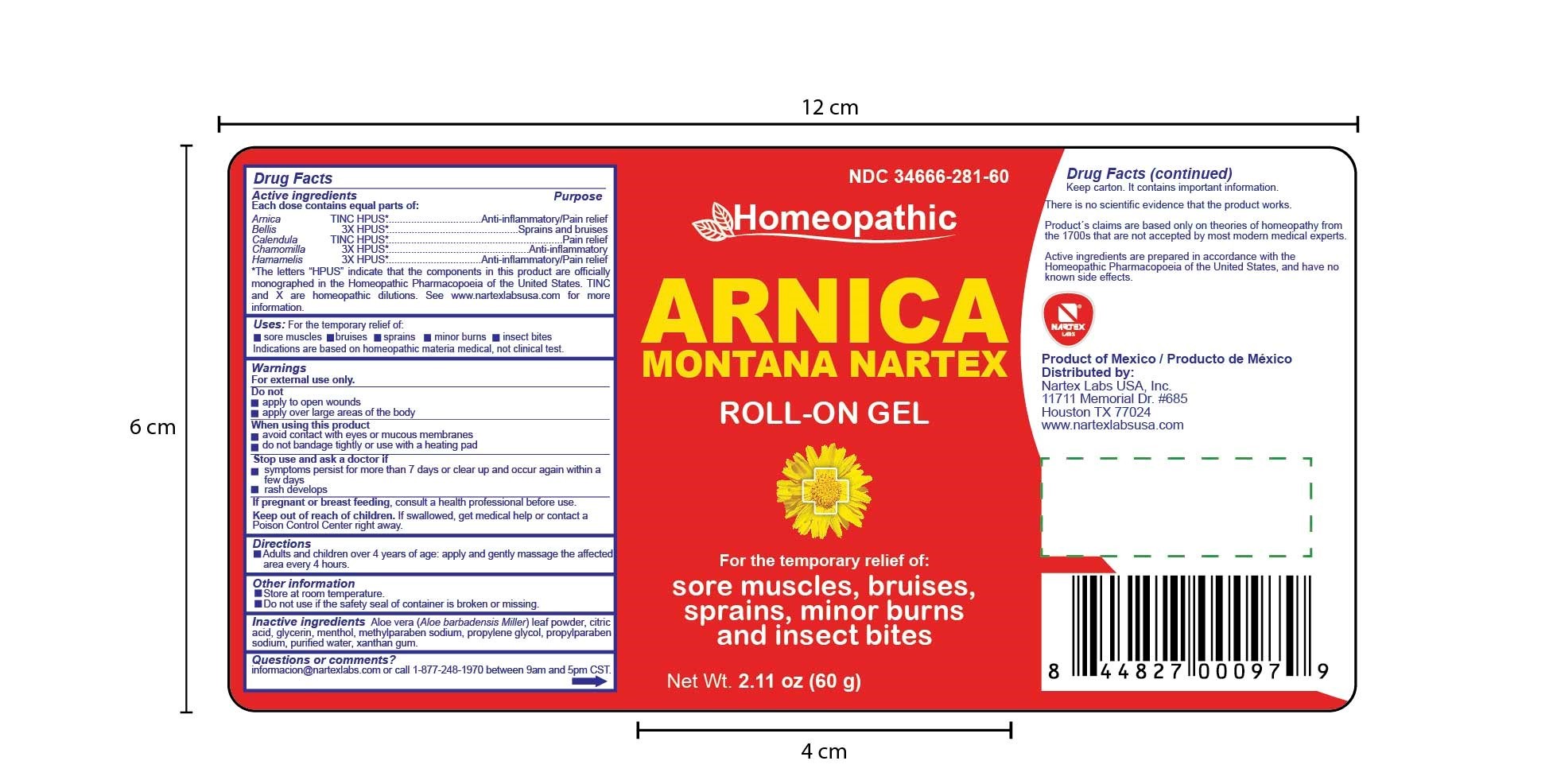 DRUG LABEL: Arnica Montana Nartex
NDC: 34666-281 | Form: GEL
Manufacturer: Nartex Laboratorios Homeopaticos SA DE CV
Category: homeopathic | Type: HUMAN OTC DRUG LABEL
Date: 20190412

ACTIVE INGREDIENTS: ARNICA MONTANA 1 [hp_X]/1 1; BELLIS PERENNIS 3 [hp_X]/1 1; CALENDULA OFFICINALIS WHOLE 1 [hp_X]/1 1; MATRICARIA CHAMOMILLA 3 [hp_X]/1 1; HAMAMELIS VIRGINIANA WHOLE 3 [hp_X]/1 1
INACTIVE INGREDIENTS: ANHYDROUS CITRIC ACID; GLYCERIN; WATER; ALOE VERA LEAF; MENTHOL; METHYLPARABEN SODIUM; PROPYLPARABEN SODIUM; XANTHAN GUM

Arnica Montana - Roll on

Active Ingredients

Arnica TINC HPUS*

Bellis 3X HPUS*

Calendula HPUS*

Chamomila 3X HPUS*

Hamamelis 3x HPUS*

Purpose

Arnica TINC HPUS*...............Anti-inflammatory/Pain Relief

Bellis 3X HPUS*.....................Sprains and Bruises

Calendula HPUS*..................Pain Relief

Chamomila 3X HPUS*..........Anti-inflammatory

Hamamelis 3x HPUS*............Anti-inflammatory/Pain Relief

*The letters HPUS indicate that the components in this product are officially monographed in the Homeopathic Pharmacopoeia of the United States. TINC and X are homeopathic dilutions. See www.nartexlabsusa.com for more information.

Uses

For the temporary relief of:

- sore muscles
- bruises
- sprains
- minor burns
- insect bites

Indications are based on homeopathic materia medica, not clnical tests.

Warnings

For External Use only

Do not:

- apply to open wounds
- apply over large areas of the body

When using this product

- avoid contact with eyes or mucous membranes
- do not bandage tightly or use with a heating pad

Stop use and ask doctor if:

- symptoms persis for more than 7 days or clear up and occur again within a few days
- rash develops

PREGNANCY OR BREAST FEEDING

If pregnant or breastfeeding, consult a health professional before use.

Keep out of reach of children. If swalled, get medical help or contact a Poison Control Center right away.

Directions

Adults and Children over 4 years of age: apply and gently massage the affected area every 4 hours.

Other Information

- Store at room temperature
- Do not use if the safety seal of container is broken or missing.

Inactive Ingredients

Aler Vera (Aloe barbadensis Miller) leaf powder, citric acid, glycerin, menthol, methylparaben sodium, propylene glycol, propylparaben sodium, purified water, xanthan gum

Questions or Comments?

infromaction@nartexlabs.com or call 1-877-248-1970 between 9am and 5pm CST.

There is no scientific evidence that the product works.

Product's claims are based only on theories of homepathy from the 1700's that are not accepted by most modern medical experts.

Active ingredients are prepared in accordance with the Homeopathic Pharmacopoeia of the United States, and have no known side effects.

Product of Mexico / Producto de Mexico

Distributed by:

Nartex Labs USA, inc

11711 Memorial Dr. # 685

Houston TX, 77024

www.nartexlabsusa.com

PACKAGE LABEL

HOMEOPATHIC

ARNICA

MONTANA NARTEX

ROLL-ON GEL

For the temporary relief of:

sore muscles, bruises, sprains, minor burns and insect bites.

Net Wt. 2.11 oz (60 g)